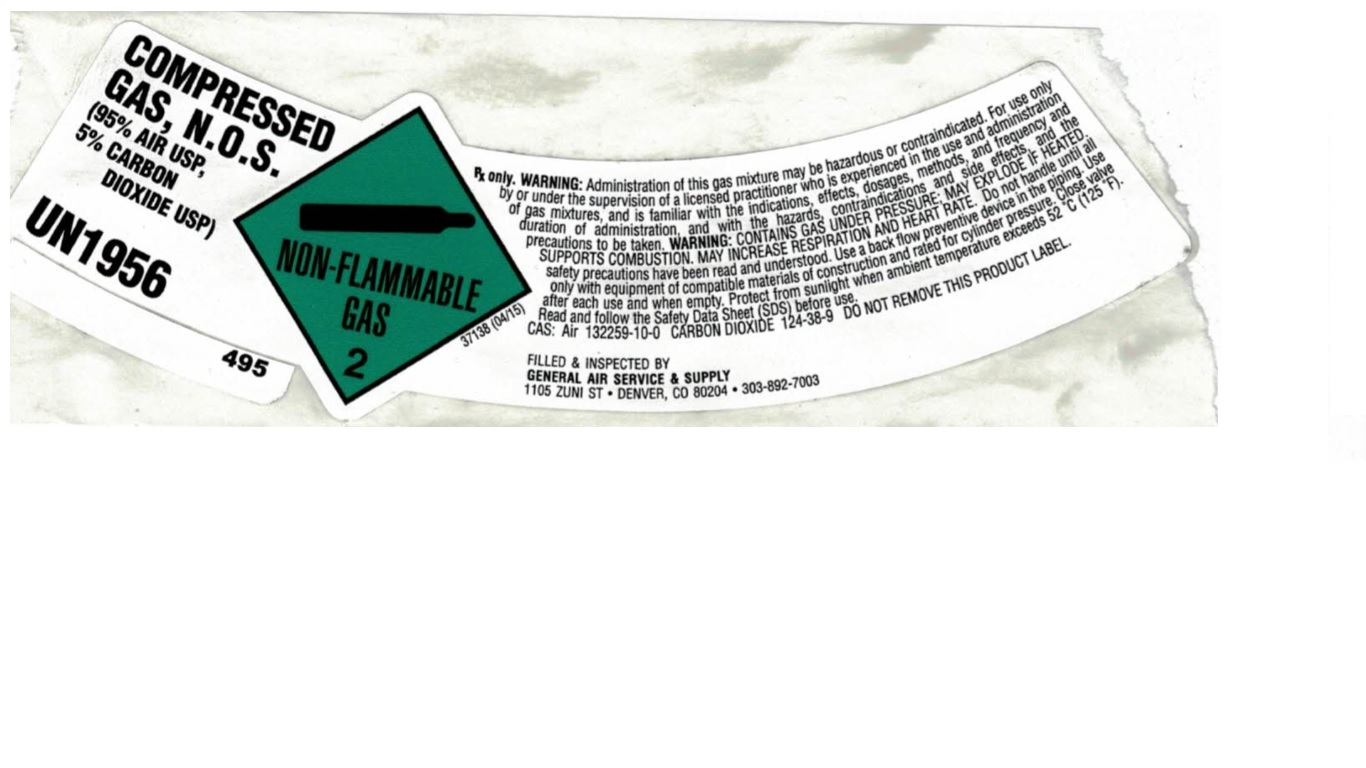 DRUG LABEL: Carbon Dioxide Air Mixture
NDC: 21220-157 | Form: GAS
Manufacturer: General Air Service & Supply Co
Category: prescription | Type: HUMAN PRESCRIPTION DRUG LABEL
Date: 20251126

ACTIVE INGREDIENTS: CARBON DIOXIDE 50 mL/1 L
INACTIVE INGREDIENTS: OXYGEN 950 mL/1 L

carbon dioxide air mixture

PACKAGE LABEL

COMPRESSED GAS, N.O.S. (95% AIR USP, 5% CARBON DIOXIDE USP) UN1956
NON-FLAMMABLE GAS 2 37138 (R04/06)
Rx only WARNING: Administration of this gas mixture may be hazardous or contraindicated. For use only by or under the supervision of a licensed practitioner who is experienced in the use and administration of gas mixtures, and is familiar with the indications, effects, dosages, methods, and frequency and duration of administration and with the hazards, contraindications and side effects and the precautions to be taken. CAUTION: HIGH PRESSURE GAS. MAY ACCELERATE COMBUSTION. CAN INCREASE RESPIRATION AND HEART RATE. Keep oil and grease away. Store and use with adequate ventilation. Use only with equipment cleaned for oxygen service and rated for cylinder pressure. Use a back flow preventive device in the piping. Cylinder temperature should not exceed 52C (125F). Open valve slowly. Close valve after each use and when empty. Use in accordance with the Material Safety Data Sheet (MSDS). FIRST AID: IF INHALED, remove to fresh air. If not breathing, give artificial respiration. If breathing is difficult, give oxygen. Call a physician. AIR CAS 132259-10-0 CARBON DIOXIDE CAS: 124-38-9 DO NOT REMOVE THIS PRODUCT LABEL
FILLED and INSPECTED BY GENERAL AIR SERVICE and SUPPLY DENVER, CO 80204 303-892-7003